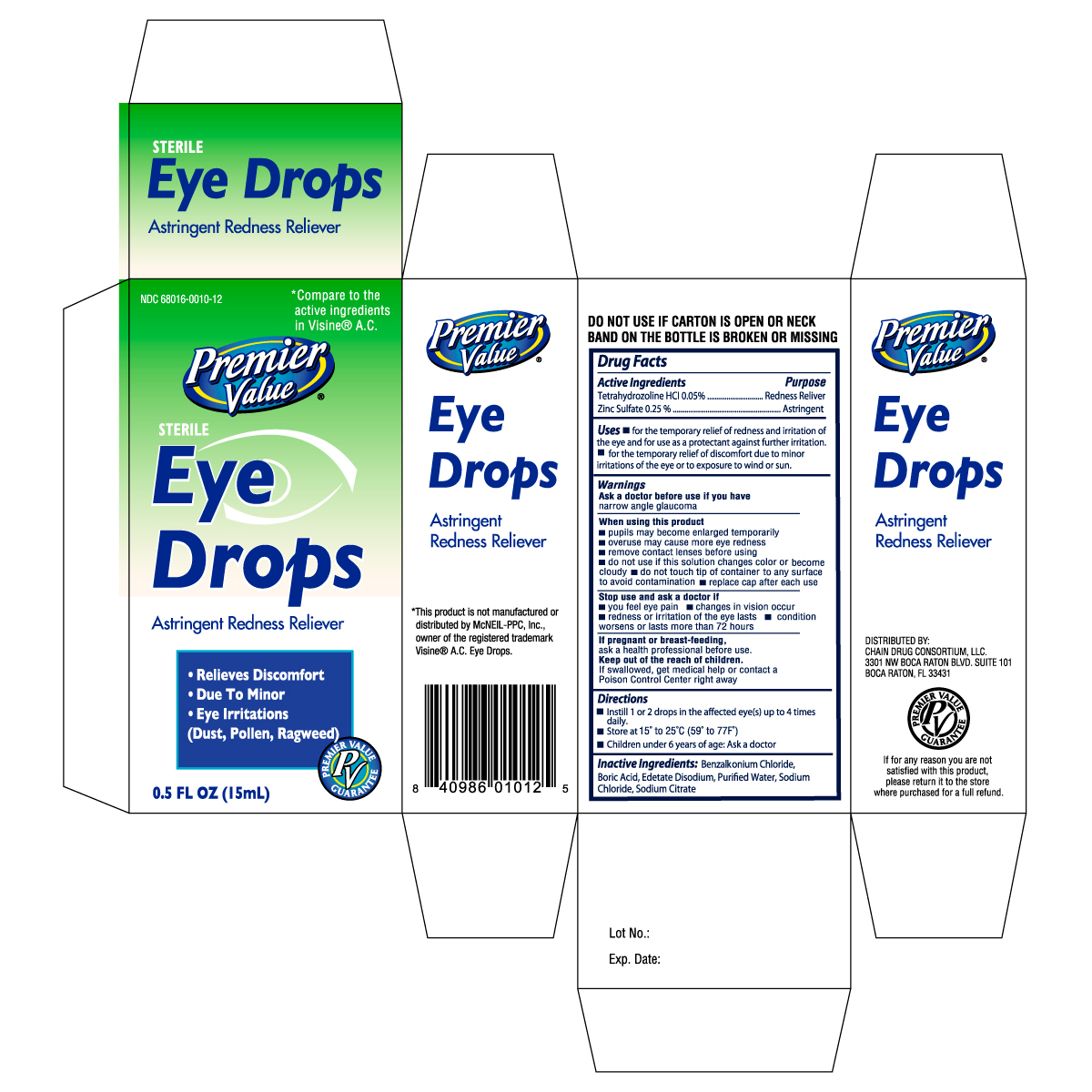 DRUG LABEL: PREMIER VALUE EYE AC
NDC: 11716-0103 | Form: SOLUTION
Manufacturer: HANLIM PHARM. CO., LTD.
Category: otc | Type: HUMAN OTC DRUG LABEL
Date: 20101102

ACTIVE INGREDIENTS: TETRAHYDROZOLINE HYDROCHLORIDE 0.5 mg/1 mL; ZINC SULFATE 2.5 mg/1 mL
INACTIVE INGREDIENTS: BENZALKONIUM CHLORIDE; BORIC ACID; EDETATE DISODIUM; WATER; SODIUM CHLORIDE; SODIUM CITRATE

Drug Facts

Active Ingredients Purpose

Tetrahydrozoline HCL 0.05% ...........................................................Redness Reliever

Zinc Sulfate 0.25% .........................................................................Astringent

Uses

- for the temporary relief of redness and irritation of the eye and for use as a protectant against further irritation.
- for the temporary relief of discomfort due to minor irritations of the eye or to exposure to wind or sun.

Warnings

Ask a doctor before use if you have narrow angle glaucoma

When using this product

- pupils may become enlarged temporarily
- overuse may cause more eye redness
- remove contact lenses before using
- do not use if this solution changes color or become cloudy
- do not touch tip of container to any surface to avoid contamination
- replace cap after each use

Stop use and ask a doctor if

- you feel eye pain
- changes in vision occur
- redness or irritation of the eye lasts
- condition worsens or lasts more than 72 hours

PREGNANCY OR BREAST FEEDING

If pregnant or breast-feeding, ask a health professional before use.

Keep out of the reach of children.

If swallowed, get medical help or contact a Poison Control Center right away.

Directions

- Instill 1 or 2 drops in the affected eye(s) up to 4 times daily
- Store at 15o to 25oC (59o to 77oF)
- Children under 6 years of age: Ask a doctor

INACTIVE INGREDIENT

Inactive ingredients: Benzalkonium Chloride, Boric Acid, Edetate Disodium, Purified Water, Sodium Chloride, Sodium Citrate

DOSAGE AND ADMINISTRATION

Distributed By:

Chain Drug Consortium, LLC.

3301 NW Boca Raton Blvd. Suite 101

Boca Raton, FL 33431

PACKAGE LABEL

Enter section text here